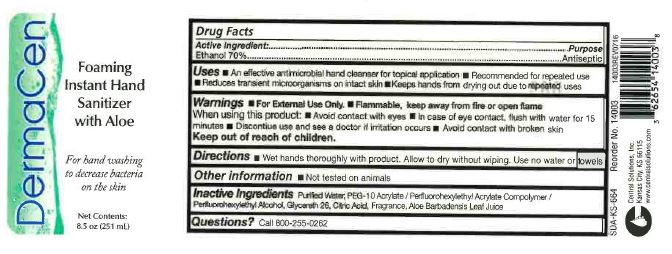 DRUG LABEL: DERMACEN FOAMING INSTANT HAND SANITIZER WITH ALOE
NDC: 62654-149 | Form: SOLUTION
Manufacturer: Central Solutions Inc
Category: otc | Type: HUMAN OTC DRUG LABEL
Date: 20241209

ACTIVE INGREDIENTS: ALCOHOL 70 mL/100 mL
INACTIVE INGREDIENTS: CITRIC ACID MONOHYDRATE; ALOE VERA LEAF; WATER; PEG-10 ACRYLATE/PERFLUOROHEXYLETHYL ACRYLATE COPOLYMER; GLYCERIN

Drug Facts 62654-149

Active Ingredient

Ethanol 70%

Purpose

Antiseptic

Uses

- An effective antimicrobial hand cleanser for topical application
- Recommended for repeated use
- Reduces transient microorganisms on intact skin
- Keeps hands from drying out due to repeated uses

Warnings

- For External Use Only
- Flammable, keep away from fire or open flame

When using this product:

- Avoid contact with eyes
- In case of eye contact, flush with water for 15 minutes

DO NOT USE

- Discontinue use and see a doctor if irritation occurs
- Avoid contact with broken skin

Keep out of reach of children.

Directions

Wet hands thoroughly with product. Allow to dry without wiping. Use no water or towels

Other information

Not tested on animals

Inactive Ingredients

Purified Water, PEG-10 Acrylate/Perfluorohexylethyl Acrylate Compolymer/Perfluorohexyethyl Alcohol, Glycereth 26, Citric Acid, Fragrance, Aloe Barbadensis Leaf Juice

Questions?

Call 800-255-0262

PACKAGE LABEL

DermaCen

Foaming

Instant Hand

Sanitizer

with Aloe

For hand washing

to decrease bacteria

on the skin

Net Contents

8.5 oz (251 mL)